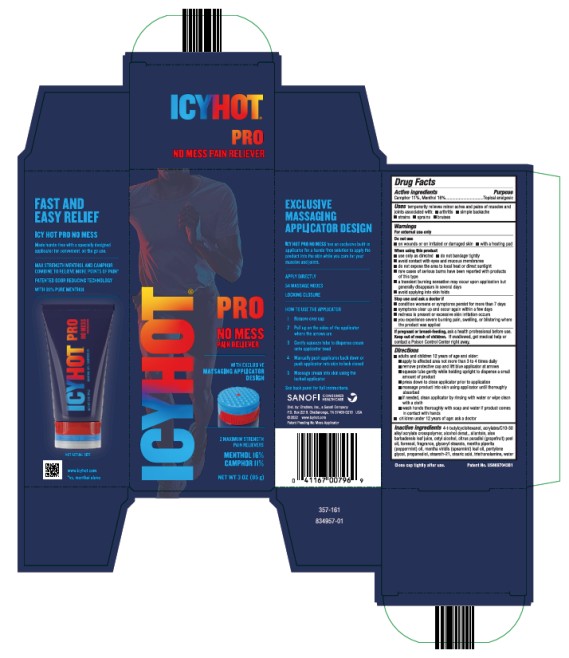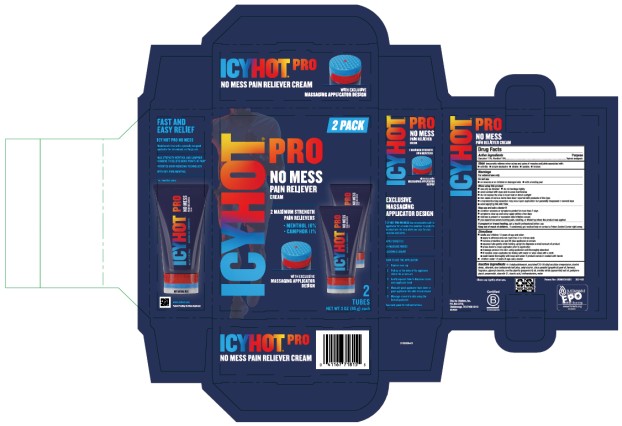 DRUG LABEL: Icy Hot Pro No-Mess
NDC: 41167-0079 | Form: CREAM
Manufacturer: Chattem, Inc.
Category: otc | Type: HUMAN OTC DRUG LABEL
Date: 20250226

ACTIVE INGREDIENTS: CAMPHOR (SYNTHETIC) 11 g/100 g; MENTHOL 16 g/100 g
INACTIVE INGREDIENTS: 4-TERT-BUTYLCYCLOHEXANOL; ALCOHOL; ALLANTOIN; ALOE VERA LEAF; CETYL ALCOHOL; GRAPEFRUIT OIL; FARNESOL; GLYCERYL STEARATE; PEPPERMINT OIL; SPEARMINT OIL; PENTYLENE GLYCOL; PROPANEDIOL; STEARETH-21; STEARIC ACID; TROLAMINE; WATER; ACRYLATES/C10-30 ALKYL ACRYLATE CROSSPOLYMER (60000 MPA.S)

Icy Hot Pro No Mess Pain Reliever

ICY HOT PRO NO MESS

Drug Facts

Active ingredients

Camphor 11%, Menthol 16%

Purpose

Topical analgesic

Uses

temporarily relieves minor aches and pains of muscles and joints associated with: ■ arthritis ■ simple backache ■ strains ■ sprains ■ bruises

Warnings

For external use only

Do not use

■ on wounds or on irritated or damaged skin

■ with a heating pad

When using this product

■ use only as directed

■ do not bandage tightly

■ avoid contact with eyes and mucous membranes

■ do not expose the area to local heat or direct sunlight

■ rare cases of serious burns have been reported with products of this type

■ a transient burning sensation may occur upon application but generally disappears in several days

■ avoid applying into skin folds

Stop use and ask a doctor if

■ condition worsens or symptoms persist for more than 7 days

■ symptoms clear up and occur again within a few days

■ redness is present or excessive skin irritation occurs

■ you experience severe burning pain, swelling, or blistering where the product was applied

Keep out of reach of children.

If swallowed, get medical help or contact a Poison Control Center right away.

Directions

- adults and children 12 years of age and older:
  ■ apply to affected area not more than 3 to 4 times daily
  ■ remove protective cap and lift blue applicator at arrows
  ■ squeeze tube gently while holding upright to dispense a small amount of product
  ■ press down to close applicator prior to application
  ■ massage product into skin using applicator until thoroughly absorbed
  ■ if needed, clean applicator by rinsing with water or wipe clean with a cloth.
  ■ wash hands thoroughly with soap and water if product comes in contact with hands
- children under 12 years of age: ask a doctor

Inactive ingredients

4-t-butylcyclohexanol, acrylates/C10-30 alkyl acrylate crosspolymer, alcohol denat., allantoin, aloe barbadensis leaf juice, cetyl alcohol, citrus paradisi (grapefruit) peel oil, farnesol, fragrance, glyceryl stearate, mentha piperita (peppermint) oil, mentha viridis (spearmint) leaf oil, pentylene glycol, propanediol, steareth-21, stearic acid, triethanolamine, water

Close cap tightly after use.

PRINCIPAL DISPLAY PANEL

ICY HOT
PRO
NO MESS
Pain reliever
NET WT 3 OZ (85 g)

PRINCIPAL DISPLAY PANEL

ICY HOT
PRO
NO MESS
Pain reliever
Cream
2 Pack
NET WT 3 OZ (85 g)